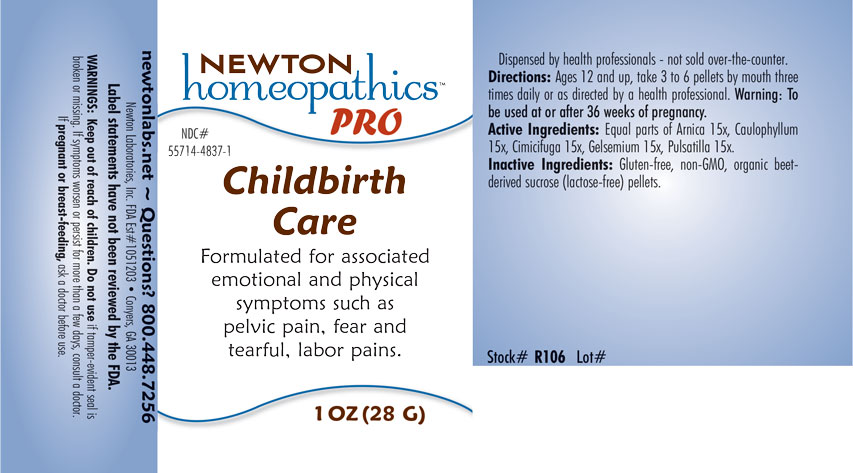 DRUG LABEL: Childbirth Care
NDC: 55714-4837 | Form: PELLET
Manufacturer: Newton Laboratories, Inc.
Category: homeopathic | Type: HUMAN OTC DRUG LABEL
Date: 20201202

ACTIVE INGREDIENTS: ARNICA MONTANA 15 [hp_X]/1 g; BLACK COHOSH 15 [hp_X]/1 g; GELSEMIUM SEMPERVIRENS ROOT 15 [hp_X]/1 g; ANEMONE PULSATILLA 15 [hp_X]/1 g; CAULOPHYLLUM THALICTROIDES ROOT 15 [hp_X]/1 g
INACTIVE INGREDIENTS: SUCROSE

Childbirth 4837P

INDICATIONS & USAGE SECTION

Formulated for associated emotional and physical symptoms such as pelvic pain, fear and tearful, labor pains.

DOSAGE & ADMINISTRATION SECTION

Directions: Ages 12 and up, take 6 drops by mouth three times daily or as directed by a health professional. Warning: To be used at or after 36 weeks of pregnancy.

OTC - ACTIVE INGREDIENT SECTION

Equal parts of Arnica montana 15x, Caulophyllum thalictroides 15x, Cimicifuga racemosa 15x, Gelsemium sempervirens 15x, Pulsatilla 15x.

OTC - PURPOSE SECTION

Formulated for associated emotional and physical symptoms such as pelvic pain, fear, and tearful, labor pains.

INACTIVE INGREDIENT SECTION

Inactive Ingredients: Gluten-free, non-GMO, organic beet-derived sucrose (lactose-free) pellets.

QUESTIONS SECTION

newtonlabs.net - Questions? 800.448.7256

Newton Laboratories, Inc. FDA Est # 1051203 Conyers, GA 30013

WARNINGS SECTION

WARNINGS: Keep out of reach of children. Do not use if tamper-evident seal is broken or missing. If symptoms worsen or persist for more than a few days, consult a doctor. If pregnant or breast-feeding, ask a doctor before use.

OTC - PREGNANCY OR BREAST FEEDING SECTION

If pregnant or breast-feeding, ask a doctor before use.

OTC - KEEP OUT OF REACH OF CHILDREN SECTION

Keep out of reach of children.